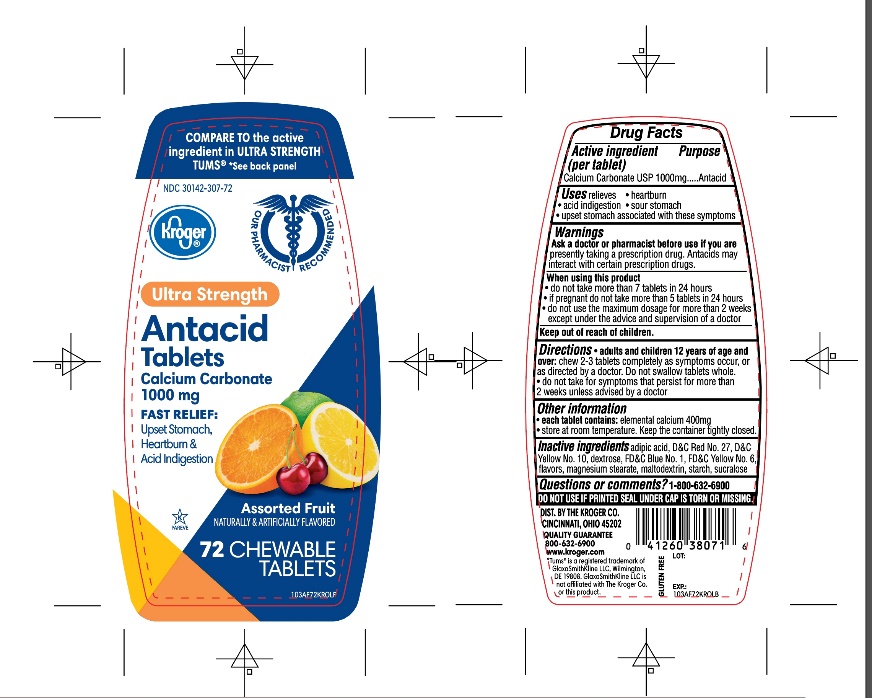 DRUG LABEL: Kroger Ultra Strength

NDC: 30142-307 | Form: TABLET, CHEWABLE
Manufacturer: KROGER COMPANY
Category: otc | Type: HUMAN OTC DRUG LABEL
Date: 20250801

ACTIVE INGREDIENTS: CALCIUM CARBONATE 1000 mg/1 1
INACTIVE INGREDIENTS: ADIPIC ACID; D&C RED NO. 27; D&C YELLOW NO. 10; DEXTROSE, UNSPECIFIED FORM; FD&C BLUE NO. 1; FD&C YELLOW NO. 6; MAGNESIUM STEARATE; MALTODEXTRIN; STARCH, CORN; SUCRALOSE

Ultra Strength Antacid Calcium Carbonate 72 Chewable Tablets

Active ingredient (per tablet)

Calcium Carbonate USP 1000mg

Purpose

Antacid

Uses

relieves

- heartburn
- acid indigestion
- sour stomach
- upset stomach associated with these symptoms

Warnings

Ask a doctor or pharmacist before use if you arepresently taking a prescription drug. Antacids may interact with certain prescription drugs.

When using this product

- do not take more than 7 tablets in 24 hours
- if pregnant do not take more than 5 tablets in 24 hours
- do not use the maximum dosage for more than 2 weeks except under the advice and supervision of a doctor.

Directions

- adults and children 12 years of age and over:chew 2-3 tablets as symptoms occur, or as directed by a doctor
- do not take for symptoms that persist for more than 2 weeks unless advised by a doctor

Other information

- each tablet contains: elemental calcium 400mg
- Store at room temperature. Keep the container tightly closed.

Inactive ingredients

adipic acid, D&C Red No. 27, D&C Yellow No. 10, dextrose, FD&C Blue No. 1, FD&C Yellow No. 6, flavors, magnesium stearate, maltodextrin, starch, sucralose.

Questions or comments?

1-800-632-6900

Safety sealed: Do not use if printed seal under cap is torn or missing

Package/Label Principal Display Panel

NDC 30142-307-72

Kroger®

FAST RELIEF OF UPSET STOMACH, HEARTBURN AND ACID INDIGESTION

COMPARE TO the active ingredient in TUMS®ULTRA STRENGTH

See back panel

ULTRA STRENGTH

Antacid Tablets

Antacid/Calcium Supplement

CALCIUM CARBONATE 1000 mg

Assorted Fruit Flavor

Naturally and Artificially Flavored

72 CHEWABLE TABLETS

K PAREVE

Our Pharmacists Recommend

GLUTEN- FREE

DISTRIBUTED BY:

THE KROGER CO. CINCINNATI, OHIO 45202

1800-632-6900

www.kroger.com

*Tums® is registered trademark of GlaxoSmithKline LLC, GlaxoSmithKline LLC is not affiliated with The Kroger Co. or this product.